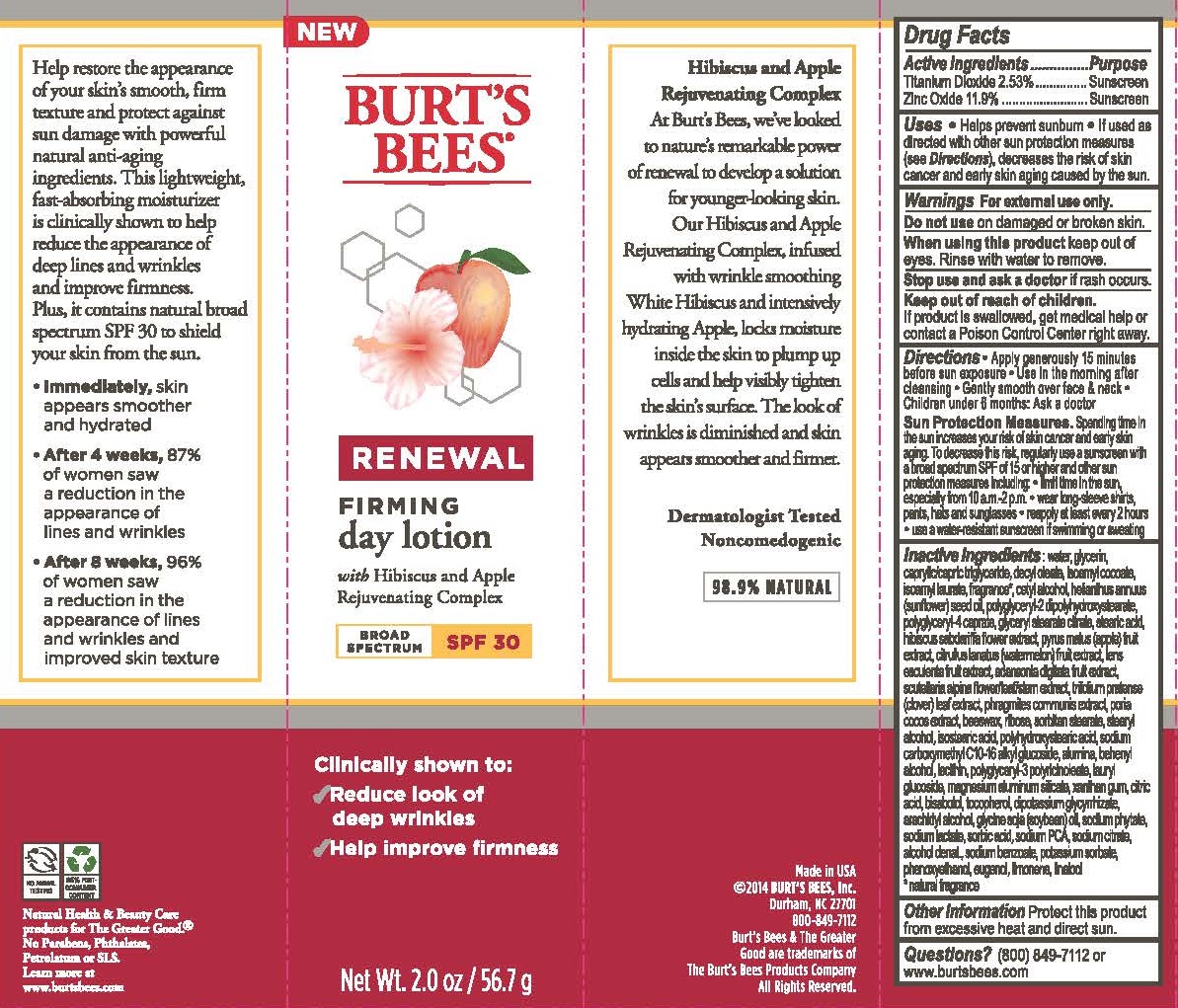 DRUG LABEL: Renewal Firming Day
NDC: 26052-027 | Form: LOTION
Manufacturer: BURT'S BEES, INC.
Category: otc | Type: HUMAN OTC DRUG LABEL
Date: 20150618

ACTIVE INGREDIENTS: TITANIUM DIOXIDE 2.53 g/100 g; ZINC OXIDE 11.9 g/100 g
INACTIVE INGREDIENTS: POLYHYDROXYSTEARIC ACID (2300 MW); YELLOW WAX; RIBOSE, D-; ALUMINUM OXIDE; DOCOSANOL; LECITHIN, SOYBEAN; LAURYL GLUCOSIDE; ANHYDROUS CITRIC ACID; .ALPHA.-BISABOLOL, (+/-)-; LENS CULINARIS FRUIT; SODIUM LACTATE; SODIUM BENZOATE; POTASSIUM SORBATE; GLYCERIN; ISOAMYL LAURATE; POLYGLYCERYL-2 DIPOLYHYDROXYSTEARATE; CETYL ALCOHOL; GLYCERYL STEARATE CITRATE; STEARIC ACID; PHENOXYETHANOL; STEARYL ALCOHOL; ISOSTEARIC ACID; MEDIUM-CHAIN TRIGLYCERIDES; DECYL OLEATE; ISOAMYL COCOATE; WATER; SUNFLOWER OIL; SORBITAN MONOSTEARATE; XANTHAN GUM; TOCOPHEROL; PHYTATE SODIUM; ARACHIDYL ALCOHOL; SOYBEAN OIL; HIBISCUS SABDARIFFA FLOWER; SORBIC ACID; ALCOHOL; APPLE; PHRAGMITES AUSTRALIS WHOLE; FU LING; CITRULLUS LANATUS VAR. LANATUS WHOLE; MAGNESIUM ALUMINUM SILICATE; GLYCYRRHIZINATE DIPOTASSIUM; ADANSONIA DIGITATA FRUIT; SCUTELLARIA ALPINA FLOWERING TOP; SODIUM PYRROLIDONE CARBOXYLATE; TRIFOLIUM PRATENSE LEAF; SODIUM CITRATE

Renewal Firming Day Lotion SPF 30

ACTIVE INGREDIENT

Titanium Dioxide 2.53%

Zinc Oxide 11.9%

PURPOSE

Sunscreen

INDICATIONS AND USAGE

- Helps prevent sunburn
- If used as directed with other sun protection measures (see Directions), decreases the risk of skin cancer and early skin aging caused by the sun.

WARNINGS

For external use only.

Do not use on damaged or broken skin.

When using this product keep out of eyes. Rinse with water to remove.

Keep out of reach of children.

If product is swallowed, get medical help or contact a Poison Control Center right away.

Stop use and ask a doctor if rash occurs.

Directions

- Apply gemerpis;u 15 minutes before sun exposure
- Use in the morning after cleansing
- Gently smooth over face & neck
- Children under 6 months: Ask a doctor

Sun Protection Measures.

Spending time in the sun increases your risk of skin cancer and early skin aging. To decrease this risk, regularly use a sunscreen with a broad spectrum SPF of 15 or higher and other sun protection measures including:

- limit time in the sun, especially from 10 a.m. - 2 p.m.
- wear long-sleeve shirts, pants, hats and sunglasses
- reapply at least every 2 hours
- use a water-resistant sunscreen if swimming or sweating

INACTIVE INGREDIENT

water, glycerin, caprylic/capric triglyceride, decyl oleate, isoamyl cocoate, isoamyl laurate, fragrance, cetyl alcohol, helianthus annuus (sunflower) seed oil, polyglyceryl-2 dipolyhydroxystearate, polyglyceryl-4 caprate, glyceryl stearate citrate, stearic acid, hibiscus sabdariffa flower extract, pyrus malus (apple) fruit extract, adansonia digitata fruit extract, scutellaria alpina flower/leaf/stem extract, trifolium pratense (clover) leaf extract, phragmites communis extract, poria cocos extract, beeswax, ribose, sorbitan stearate, stearyl alcohol, isostearic acid, polyhydroxystearic acid, sodium carboxymethyl C10-16 alkyl glucoside, alumina, behenyl alcohol, lesichin, polyglyceryl-3 polyricinoleate, lauryl glucoside, magnesium aluminum silicate, xanthan gum, citric acid, bisabolol, tocopherol, dipotassium glycyrrhizate, arachidyl alcohol, glycine soja (soybean) oil, sodium phytate, sodium lactate, sorbic acid, sodium PCA, sodium citrate, alcohol denat., sodium benzoate, potassium sorbate, phenoxyethanol, eugenol, limonene, linalool.

Other Information

Protect this product from excessive heat and direct sun.

QUESTIONS

(800) 849-7112 or www.burtsbees.com

PACKAGE LABEL

BURT'S BEES

RENEWAL

FIRMING

day lotion

with Hibiscus and Apple

Rejuvinating Complex

BROAD SPECTRUM SPF 30

Clinically shown to:

- Reduce look of deep wrinkles
- Help improve firmness

Net Wt. 2.0 oz / 56.7 g